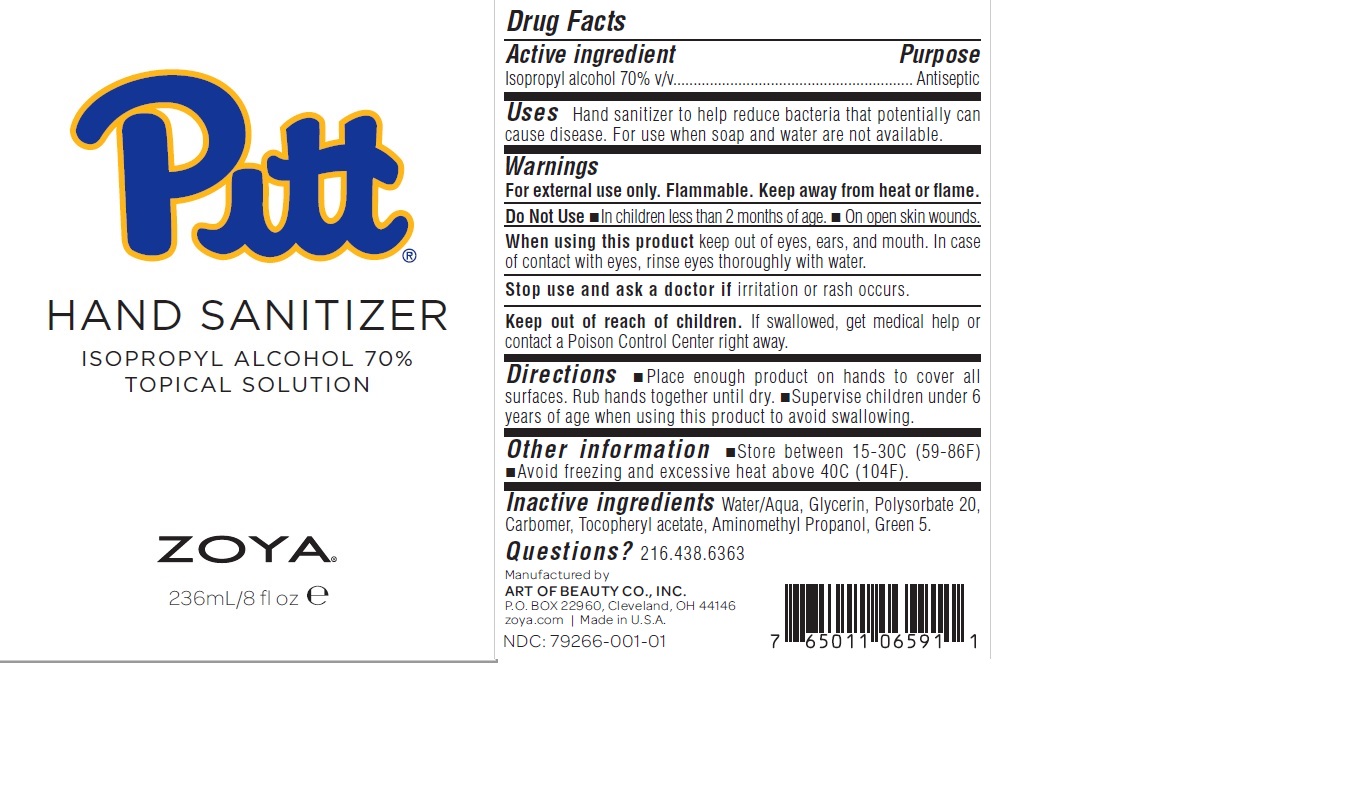 DRUG LABEL: HAND SANITIZER
NDC: 79266-001 | Form: SOLUTION
Manufacturer: University of Pittsburgh
Category: otc | Type: HUMAN OTC DRUG LABEL
Date: 20240108

ACTIVE INGREDIENTS: ISOPROPYL ALCOHOL 70 mL/100 mL
INACTIVE INGREDIENTS: POLYSORBATE 20; D&C GREEN NO. 5; GLYCERIN; .ALPHA.-TOCOPHEROL ACETATE; CARBOMER HOMOPOLYMER, UNSPECIFIED TYPE; AMINOMETHYLPROPANOL; WATER

Pitt Hand Sanitizer

Active ingredient

Isopropyl alcohol 70% v/v

Purpose

Antiseptic

Uses

Hand sanitizer to help reduce bacteria that potentially can cause disease. For use when soap and water are not available.

Warnings

For external use only. Flammable. Keep away from heat or flame.

Do not use

- In children less than 2 months of age.
- On open skin wounds.

When using this product

keep out of eyes, ears, and mouth. In case of contact with eyes, rinse eyes thoroughly with water.

Stop use and ask a doctor if

irritation or rash occurs.

Keep out of reach of children.

If swallowed, get medical help or contact a Poison Control Center right away.

Directions

- Place enough product on hands to cover all surfaces. Rub hands together until dry.
- Supervise children under 6 years of age when using this product to avoid swallowing.

Other information

- Store between 15-30C (59-86F).
- Avoid freezing and excessive heat above 40C (104F).

Inactive ingredients

Water/Aqua, Glycerin, Polysorbate 20, Carbomer, Tocopheryl acetate, Aminomethyl Propanol, Green 5.

Questions?

216.438.6363

Company Information

Manufactured by

ART OF BEAUTY CO., INC.

P.O. BOX 22960

Cleveland, OH 44146

zoya.com Made in U.S.A.

NDC: 79266-001-01

Product Packaging

Pitt

HAND SANITIZER

ISOPROPYL ALCOHOL 70%

TOPCAL SOLUTION

ZOYA

236mL/8 fl oz